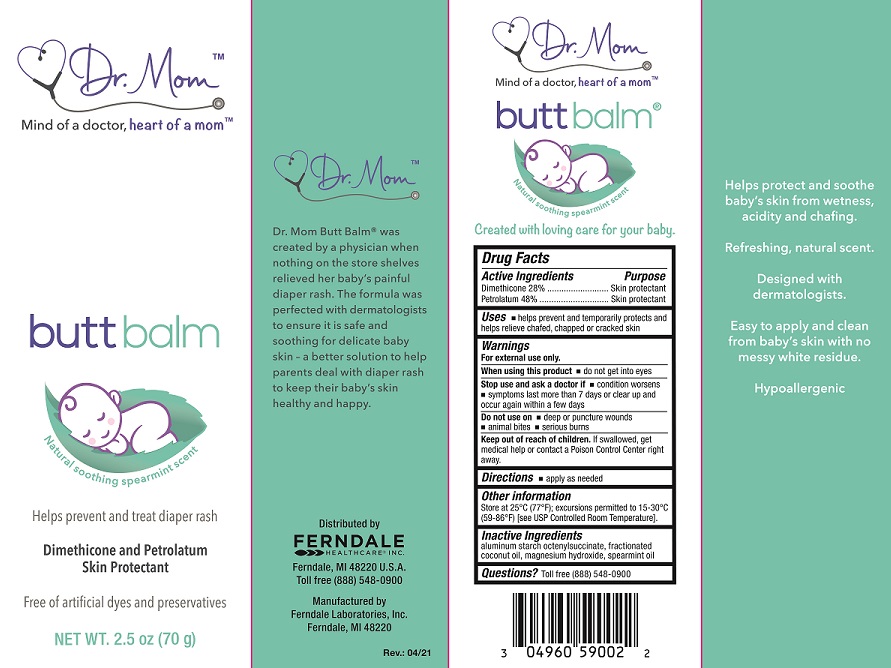 DRUG LABEL: Dr. Mom Butt Balm
NDC: 0496-0590 | Form: OINTMENT
Manufacturer: Ferndale Laboratories, Inc.
Category: otc | Type: HUMAN OTC DRUG LABEL
Date: 20240613

ACTIVE INGREDIENTS: DIMETHICONE 0.28 g/1 g; WHITE PETROLATUM 0.48 g/1 g
INACTIVE INGREDIENTS: ALUMINUM STARCH OCTENYLSUCCINATE; MEDIUM-CHAIN TRIGLYCERIDES; SPEARMINT OIL; MAGNESIUM HYDROXIDE

Dr. Mom Butt Balm

Active Ingredients

Dimethicone 28%

White Petrolatum 48%

Purpose

Dimethicone 28%..........Skin protectant

White Petrolatum 48%............Skin protectant

Uses

- helps prevent and temporarily protects and helps relieve chafed, chapped or cracked skin

Warnings

For external use only.

When using this product

- do not get into eyes

Stop use and ask a doctor if

- condition worsens
- symptoms last more than 7 days or clear up and occur again within a few days

Do not use on

- deep or puncture wounds
- animal bites
- serious burns

Keep out of reach of children.

If swallowed, get medical help or contact a Poison Control Center right away.

Directions

- apply as needed

Other information

Store at 25°C (77°F); excursions permitted to 15-30°C (59-86°F) [see USP Controlled Room Temperature].

Inactive Ingredients

aluminum starch octenylsuccinate, fractionated coconut oil, magnesium hydroxide, spearmint oil

Questions?

Toll free (888) 548-0900